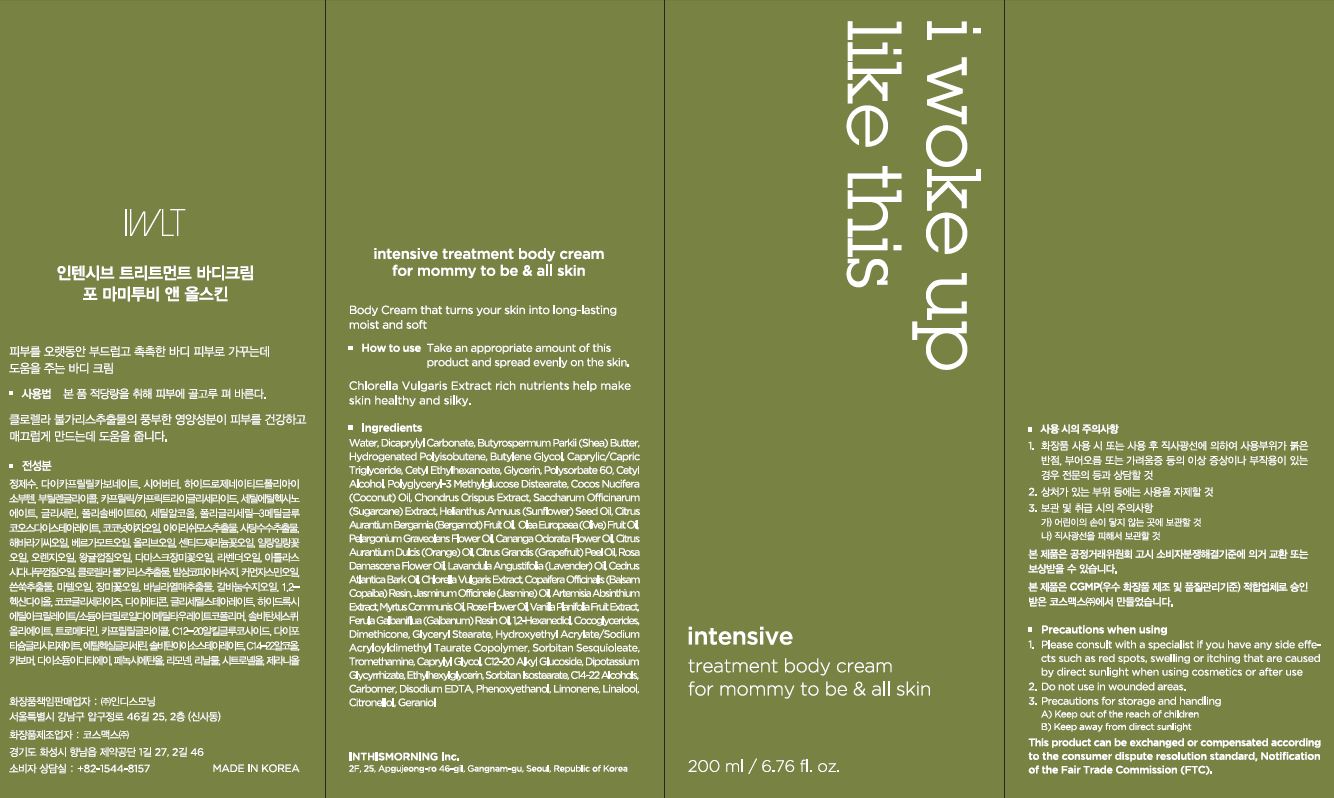 DRUG LABEL: Intensive treatment bodycream for mommy to be and all skin
NDC: 71217-0063 | Form: CREAM
Manufacturer: inthismorning co ltd
Category: otc | Type: HUMAN OTC DRUG LABEL
Date: 20230615

ACTIVE INGREDIENTS: LINALOOL, (+/-)- 0.0123856248 g/100 mL; .BETA.-CITRONELLOL, (R)- 0.0072288108 g/100 mL; GERANIOL 0.003659868 g/100 mL; LIMONENE, (+/-)- 0.0330317226 g/100 mL
INACTIVE INGREDIENTS: OLIVE OIL

Drug Facts

ACTIVE INGREDIENT

citronellol, geraniol, linalool, limonene

INACTIVE INGREDIENT

Olea Europaea (Olive) Fruit Oil
Carthamus Tinctorius (Safflower) Seed Oil
Helianthus Annuus (Sunflower) Seed Oil
Camellia Japonica Seed Oil
Macadamia Integrifolia Seed Oil
Tocopheryl Acetate
Citrus Aurantium Bergamia (Bergamot) Fruit Oil
Pelargonium Graveolens Flower Oil
Cananga Odorata Flower Oil
Cedrus Atlantica Bark Oil
Lavandula Angustifolia (Lavender) Oil
Rosa Damascena Flower Oil
Tocopherol
Copaifera Officinalis (Balsam Copaiba) Resin
Jasminum Officinale (Jasmine) Oil
Citrus Aurantium Dulcis (Orange) Oil
Artemisia Absinthium Extract
Citrus Grandis (Grapefruit) Peel Oil
Myrtus Communis Oil
Rose Flower Oil
Vanilla Planifolia Fruit Extract
Ferula Galbaniflua (Galbanum) Resin Oil

PURPOSE

intensive treatment body cream

keep out or reach of the children

INDICATIONS AND USAGE

take an appropriate amount of this product and spread evenly on the skin

WARNINGS

This product is for exeternal use only. Do not use for internal use
Storage and handling precautions
If possible, avoid direct sunlight and store in cool and area of low humidity in order to maintain the quality of the product and avoid misuse
Avoid placing the product near fire and store out in reach of children

- consult a physician in case of abnormal symptoms, such as red spots, swelling or itching, or side effects in the areas of application due to direct light during or after using the product

- do not use on wounded area

DOSAGE AND ADMINISTRATION

for external use only